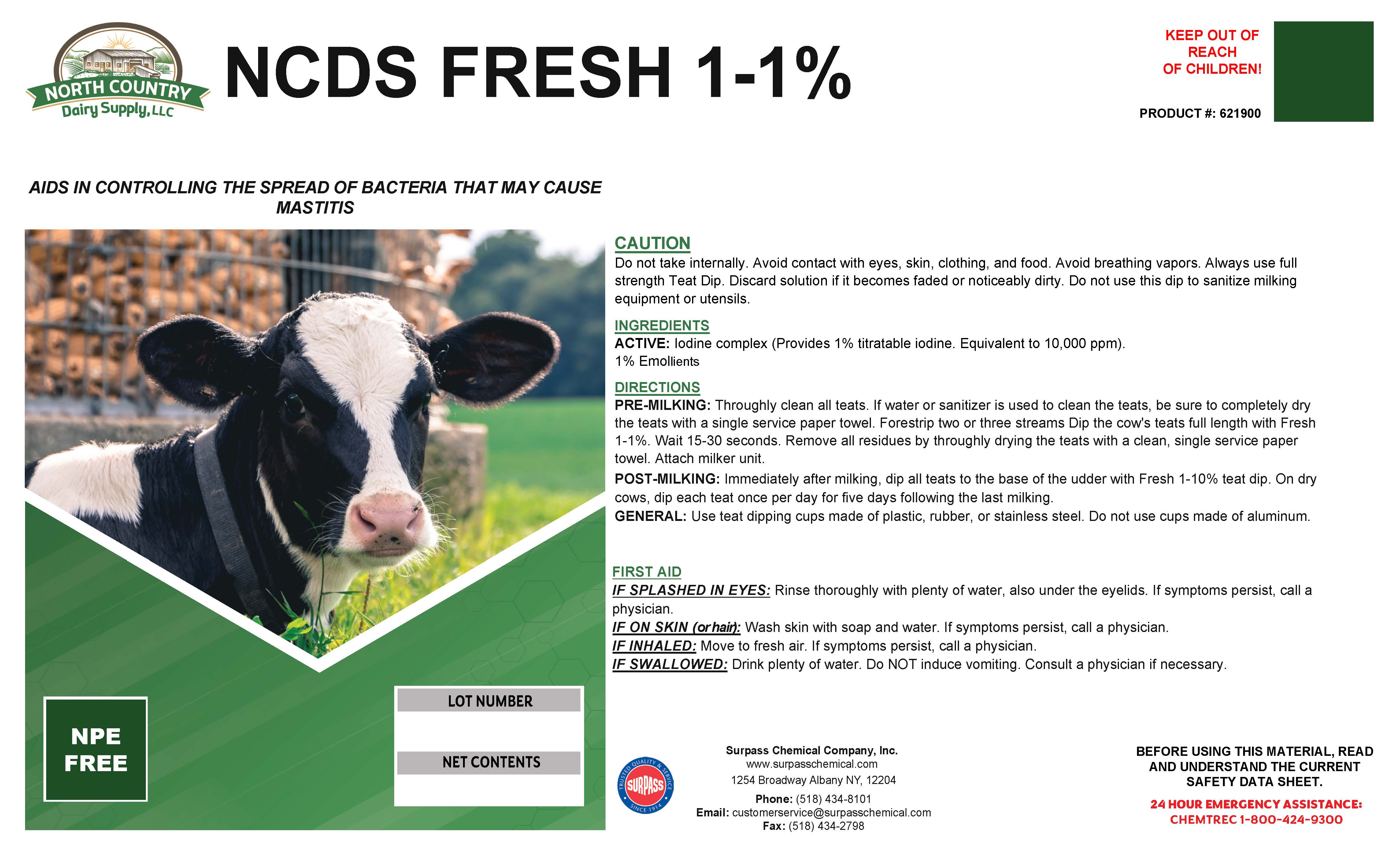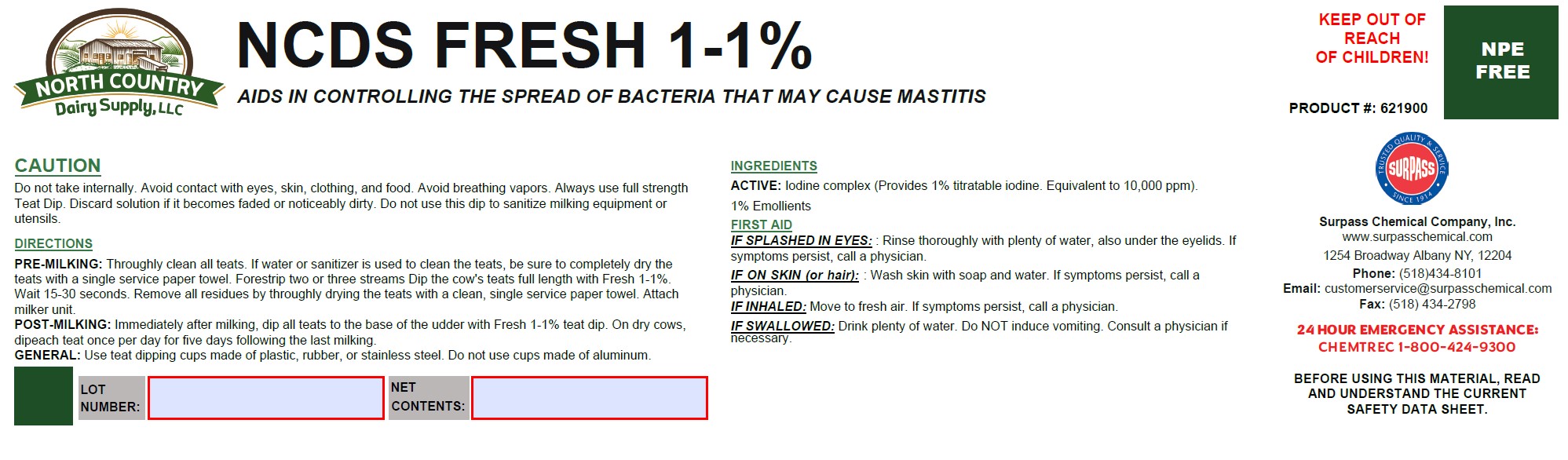 DRUG LABEL: NCDS Fresh 1-1%
NDC: 86067-0200 | Form: SOLUTION
Manufacturer: Surpass Chemical Company, Inc.
Category: animal | Type: OTC ANIMAL DRUG LABEL
Date: 20240528

ACTIVE INGREDIENTS: IODINE 0.0472 kg/1 kg
INACTIVE INGREDIENTS: WATER 0.8708 kg/1 kg; C9-11 PARETH-8 0.065 kg/1 kg; GLYCERIN .01 kg/1 kg; TRISODIUM CITRATE DIHYDRATE .07 kg/1 kg

NCDS Fresh 1-1%

DESCRIPTION

NCDS FRESH 1-1%

An aid in a complete cow care program to help control external organisms that may cause mastitis. PRODUCT #: 621900

DIRECTIONS:
PRE-MILKING: Throughly clean all teats. If water or sanitizer is used to clean the teats, be sure to completely dry the teats with a single service paper towel. Forestrip two or three streams Dip the cow's teats full length with Fresh 1-1%. Wait 15-30 seconds. Remove all residues by throughly drying the teats with a clean, single service paper towel. Attach milker unit.
POST-MILKING: Immediately after milking, dip all teats to the base of the udder with Fresh 1-10% teat dip. On dry cows, dip each teat once per day for five days following the last milking.
GENERAL: Use teat dipping cups made of plastic, rubber, or stainless steel. Do not use cups made of aluminum.

GENERAL PRECAUTIONS

CAUTION:
Do not take internally. Avoid contact with eyes, skin, clothing, and food. Avoid breathing vapors. Always use full strength Teat Dip. Discard solution if it becomes faded or noticeably dirty. Do not use this dip to sanitize milking equipment or utensils.

ACTIVE INGREDIENT

INGREDIENTS:
ACTIVE: Iodine complex (Provides 1% titratable iodine. Equivalent to 10,000 ppm).

1% Emollients

OTHER SAFETY INFORMATION

FIRST AID:
IF SPLASHED IN EYES: Rinse thoroughly with plenty of water, also under the eyelids. If symptoms persist, call a physician.
IN CASE OF CONTACT: Wash skin with soap and water. If symptoms persist, call a physician.
IF INHALED: Move to fresh air. If symptoms persist, call a physician.
IF SWALLOWED: Drink plenty of water. Do NOT induce vomiting. Consult a physician if necessary.

SAFE HANDLING WARNING

BEFORE USING THIS MATERIAL, READ AND
UNDERSTAND THE CURRENT SAFETY DATA SHEET.

Surpass Chemical Company, Inc. 24 HOUR EMERGENCY ASSISTANCE:
www.surpasschemical.com Phone: (518) 434-8101 CHEMTREC 1-800-424-9300
1254 Broadway Fax: (518) 434-2798

Albany NY, 12204 Email: customerservice@surpasschemical.com

KEEP OUT OF REACH OF CHILDREN!